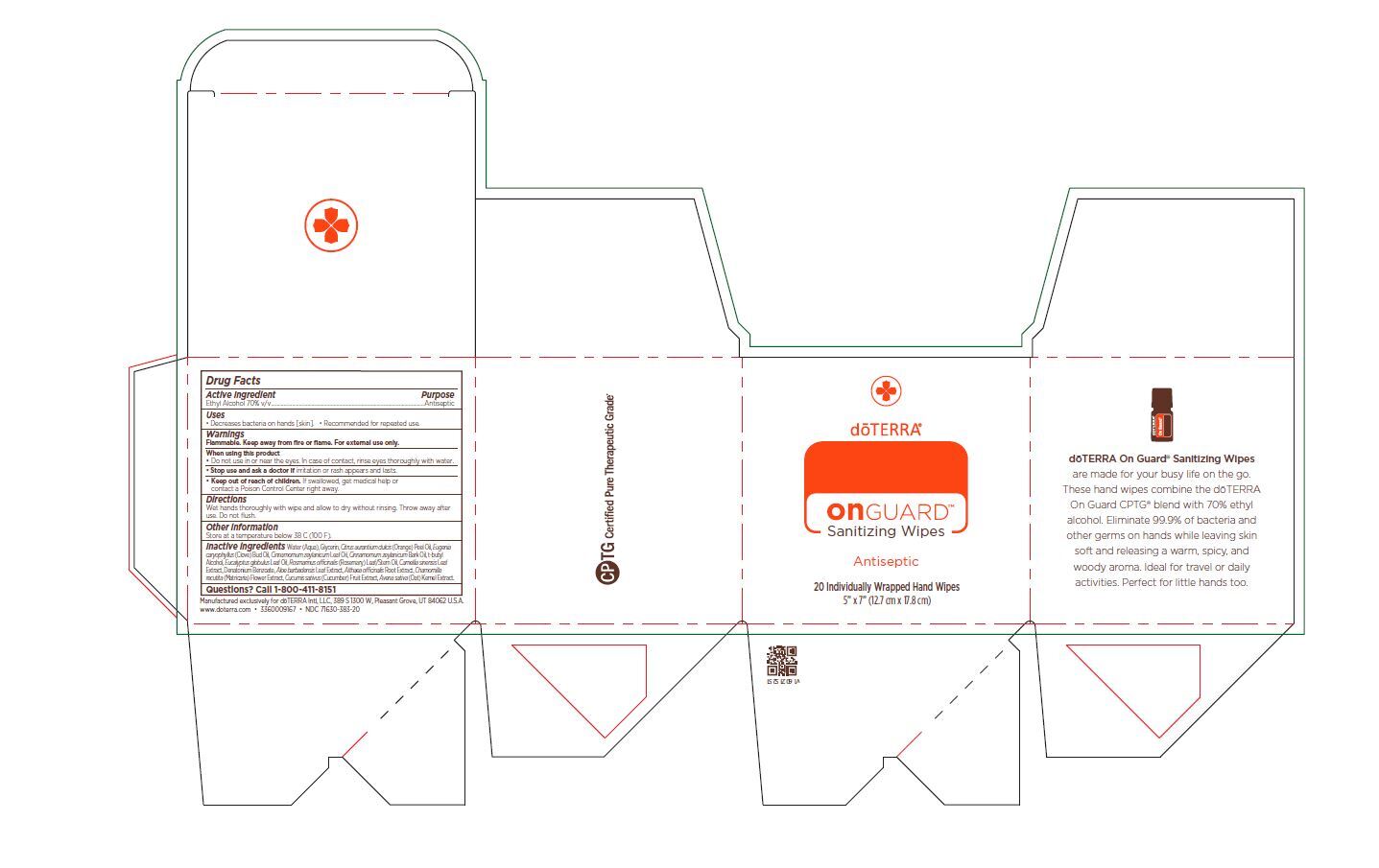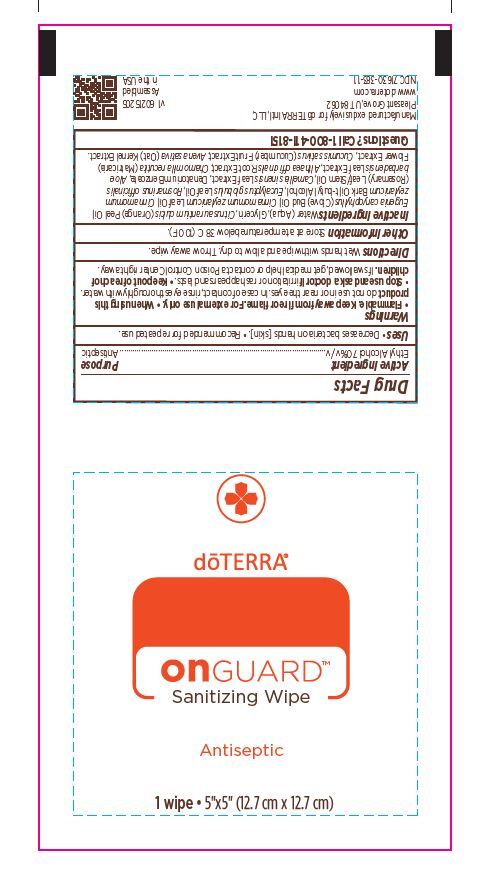 DRUG LABEL: On Guard Sanitizing Wipes
NDC: 71630-383 | Form: CLOTH
Manufacturer: doTERRA International, LLC
Category: otc | Type: HUMAN OTC DRUG LABEL
Date: 20250128

ACTIVE INGREDIENTS: ALCOHOL 70 mL/100 mL
INACTIVE INGREDIENTS: AVENA SATIVA WHOLE; DENATONIUM BENZOATE; MATRICARIA RECUTITA FLOWERING TOP; EUCALYPTUS OIL; WATER; ALOE VERA LEAF; GLYCERIN; CINNAMON LEAF OIL; ROSEMARY OIL; CLOVE OIL; CINNAMON BARK OIL; ORANGE OIL; TERT-BUTYL ALCOHOL; ALTHAEA OFFICINALIS ROOT; CUCUMIS SATIVUS WHOLE; GREEN TEA LEAF

On Guard Sanitizing Wipes (DW)

Active Ingredient(s)

Ethyl Alcohol 70% v/v. Purpose: Antiseptic

Purpose

Antiseptic, Hand Sanitizer

Use

•Decreases bacteria on hands [skin].
•Recommended for repeated use.

Warnings

For external use only. Flammable. Keep away from heat or flame

Do not use in or near the eyes. In case of contact, rinse eyes thoroughly with water

Stop use and ask a doctor if irritation or rash appears and lasts.

Keep out of reach of children. If swallowed, get medical help or contact Poison Control Center right away.

Stop use and ask a doctor if irritation or rash occurs and lasts.

Keep out of reach of children. If swallowed, get medical help or contact a Poison Control Center right away.

Directions

Wet hands thoroughly with wipe and allow to dry without rinsing. Throw away after use. Do not flush.

Other information

- Store at a temperature below 38 C (100 F).

Inactive ingredients

Water (Aqua), Glycerin, Citrus aurantium dulcis (Orange) Peel Oil, Eugenia caryophyllus (Clove) Bud Oil, Cinnamomum zeylanicum Leaf Oil, Cinnamomum zeylanicum Bark Oil, t-butyl
Alcohol, Eucalyptus globulus Leaf Oil, Rosmarinus officinalis (Rosemary) Leaf/Stem Oil, Camellia sinensis Leaf
Extract, Denatonium Benzoate, Aloe barbadensis Leaf Extract, Althaea officinalis Root Extract, Chamomilla recutita (Matricaria) Flower Extract, Cucumis sativus (Cucumber) Fruit Extract, Avena sativa (Oat) Kernel Extract.

Package Label - Principal Display Panel

20 Count NDC: 71630-383-20

Single Packet: NDC 71630-383-11